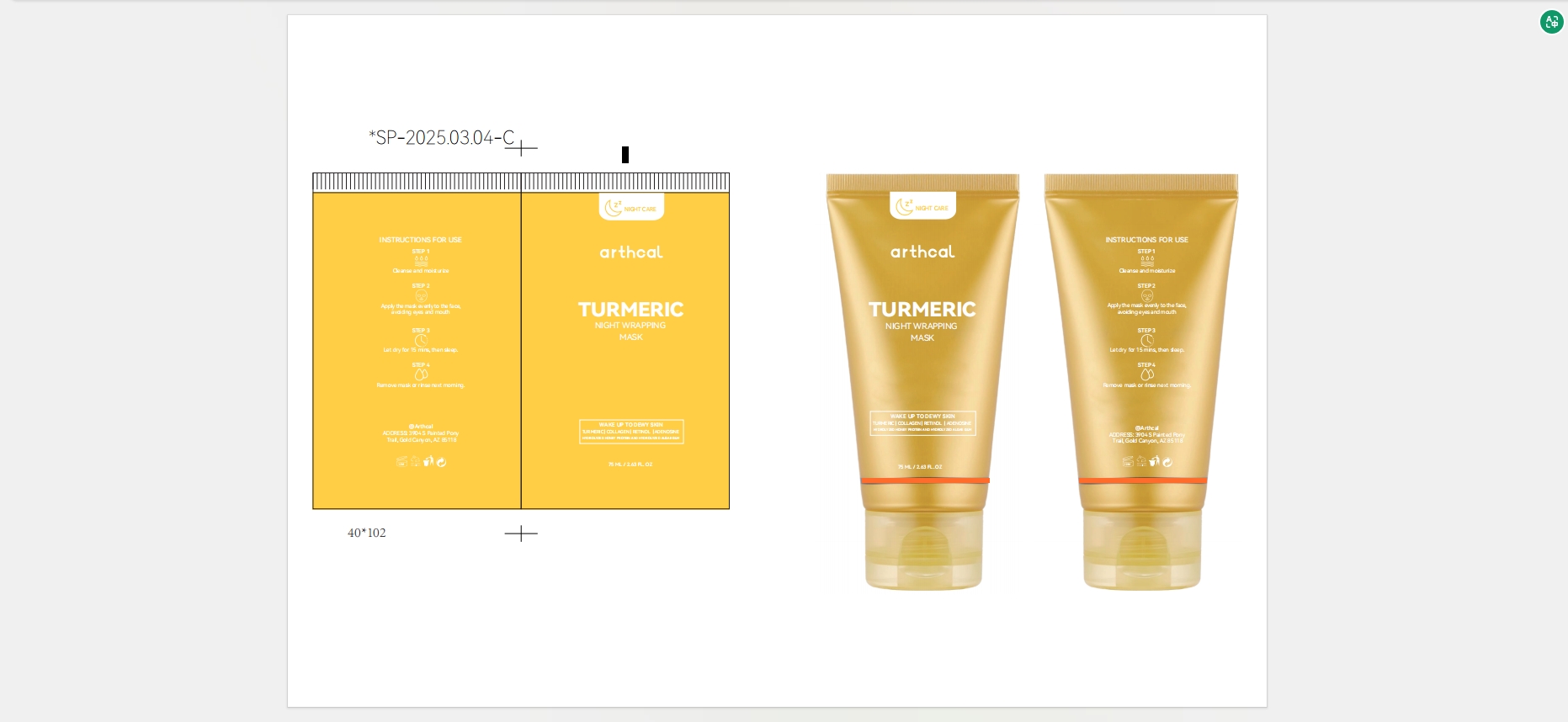 DRUG LABEL: Arthcal TURMERIC  NIGHT WRAPPING MASK
NDC: 85212-0033 | Form: GEL
Manufacturer: Beijing JUNGE Technology Co., Ltd.
Category: otc | Type: HUMAN OTC DRUG LABEL
Date: 20250430

ACTIVE INGREDIENTS: CURCUMA LONGA WHOLE 5 g/100 mL; HYDROLYSED BOVINE COLLAGEN (ENZYMATIC; 2000-5000 MW) 5 g/100 mL
INACTIVE INGREDIENTS: RETINOL 1 mL/100 mL; HYDROXYETHYLCELLULOSE 0.1 mL/100 mL; PROPOLIS CERA 1 mL/100 mL; LAMINARIA DIGITATA HYDROLYZED ALGINIC ACID 2 mL/100 mL; AQUA 65.9 mL/100 mL; OCTANEDIOL 0.1 mL/100 mL; ADENOSINE 0.1 mL/100 mL; POLYVINYL ALCOHOL 5 mL/100 mL; KOJIC ACID 2 mL/100 mL; LAURYL GLUCOSIDE 1 mL/100 mL; HYDROLYZED ELASTIN 2 mL/100 mL; SODIUM METAPHOSPHATE 0.1 mL/100 mL; 1,2-HEXANEDIOL 2 mL/100 mL; DIPROPYLENE GLYCOL 5 mL/100 mL; GLYCERETH-6 LAURATE 0.5 mL/100 mL; PECTIN 0.5 mL/100 mL; CELLULOSE GUM 0.1 mL/100 mL; SUCROSE 0.5 mL/100 mL; ETHYLHEXYLGLYCERIN 0.1 mL/100 mL; ASCORBIC ACID 1 mL/100 mL

ALARMS

Patch Test

Conduct a patch test 24 hours prior by applying a small amount behind ear or inner wrist. Discontinue if redness/itching occurs.

Contraindications

Avoid contact with eyes, open wounds, or active acne. Rinse immediately if product enters eyes.
× Compromised skin barrier (open wounds/post-op recovery)
× Pathological skin conditions (rosacea/acute eczema/herpes flare-up)
× Recent aesthetic procedures (＜6 weeks post-chemical peel/＜3 months post-laser)

Storage & Shelf Life

Store in a cool, dry place (below 25℃). Use within 6 months after opening.

Special Populations

Consult a physician before use if pregnant, breastfeeding, or with hypersensitive skin. Keep away from children.

Adverse Reactions

Discontinue and apply a cool compress if irritation persists. Seek medical attention for severe reactions.

Drying & Overnight Care

Allow the mask to dry completely before sleeping, and avoid contact with bedding or fabrics to prevent staining.

Keep out of reach of children.

INACTIVE INGREDIENT

AQUA
DIPROPYLENE GLYCOL
POLYVINYL ALCOHOL
KOJIC ACID
1,2-HEXANEDIOL
HYDROLYZED ELASTIN
HYDROLYZED ALGIN
RETINOL
ASCORBIC ACID
PROPOLIS EXTRACT
LAURYL GLUCOSIDE
GLYCERETH-6 LAURATE
PECTIN
SUCROSE
CELLULOSE GUM
HYDROXYETHYLCELLULOSE
SODIUM METAPHOSPHATE
OCTANEDIOL
ETHYLHEXYLGLYCERIN
ADENOSINE

STORAGE AND HANDLING

Keep in a dry and cool place.

DOSAGE AND ADMINISTRATION

STEP1 Cleanse and moisturize.
STEP2 Apply the mask evenly to the face, avoiding eyes and mouth.
STEP3 Let dry for 15 mins, then sleep.

STEP4 Remove mask or rinse next morning.

WHEN USING

Use a silicone brush or applicator to spread a thin, even layer over face, avoiding eye contours, lips, brows, and hairline. Translucent coverage is ideal.

STOP USE

Conduct a patch test 24 hours prior by applying a small amount behind ear or inner wrist. Discontinue if redness/itching occurs.

DO NOT USE

× Compromised skin barrier (open wounds/post-op recovery)
× Pathological skin conditions (rosacea/acute eczema/herpes flare-up)

ACTIVE INGREDIENT

CURCUMA LONGA EXTRACT, HYDROLYZED COLLAGEN

WARNINGS

Patch Test

Conduct a patch test 24 hours prior by applying a small amount behind ear or inner wrist. Discontinue if redness/itching occurs.

Contraindications

Avoid contact with eyes, open wounds, or active acne. Rinse immediately if product enters eyes.
× Compromised skin barrier (open wounds/post-op recovery)
× Pathological skin conditions (rosacea/acute eczema/herpes flare-up)
× Recent aesthetic procedures (＜6 weeks post-chemical peel/＜3 months post-laser)

Storage & Shelf Life

Store in a cool, dry place (below 25℃). Use within 6 months after opening.

Special Populations

Consult a physician before use if pregnant, breastfeeding, or with hypersensitive skin. Keep away from children.

Adverse Reactions

Discontinue and apply a cool compress if irritation persists. Seek medical attention for severe reactions.

Drying & Overnight Care

Allow the mask to dry completely before sleeping, and avoid contact with bedding or fabrics to prevent staining.

INDICATIONS AND USAGE

Directions for Use

Pre-Cleansing Routine

After cleansing, apply toner to balance skin pH, followed by a moisturizer.

Application

Use a silicone brush or applicator to spread a thin, even layer over face, avoiding eye contours, lips, brows, and hairline. Translucent coverage is ideal.

Drying & Wear Time

Allow mask to dry completely for 15 minutes before sleeping. Avoid touching the face to prevent transfer.

Morning Removal

Gently peel off the mask from the edges in the morning. Rinse with lukewarm water if residue remains. Use a damp cotton pad on stubborn areas.

Post-Treatment

Follow with a calming serum or cream to lock in hydration and enhance radiance.

PURPOSE

Wake Up to Dewy Skin